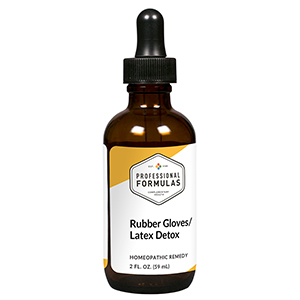 DRUG LABEL: Rubber Gloves/Latex Detox
NDC: 63083-6029 | Form: LIQUID
Manufacturer: Professional Complementary Health Formulas
Category: homeopathic | Type: HUMAN OTC DRUG LABEL
Date: 20190815

ACTIVE INGREDIENTS: NATURAL LATEX RUBBER 6 [hp_X]/59 mL; POLYURETHANE-35 (NOT MORE THAN 500 MPA.S AT 40%) 6 [hp_X]/59 mL
INACTIVE INGREDIENTS: ALCOHOL; WATER

X29

ACTIVE INGREDIENTS

Latex 6X, 12X, 30X, 60X, 100X
Lycra 6X, 12X, 30X, 60X, 100X

QUESTIONS

Professional Formulas

PO Box 2034 Lake Oswego, OR 97035

INDICATIONS

For the temporary relief of red, itchy, or irritated skin, watery eyes, throat irritation, runny nose, or sneezing due to sensitivity to or exposure to latex or lycra products.*

PURPOSE

*Claims based on traditional homeopathic practice, not accepted medical evidence. Not FDA evaluated.

WARNINGS

Consult a doctor if condition worsens or symptoms persist. Keep out of the reach of children. In case of overdose, get medical help or contact a poison control center right away. If pregnant or breastfeeding, ask a healthcare professional before use.

Keep out of the reach of children.

PREGNANCY OR BREAST FEEDING

If pregnant or breastfeeding, ask a healthcare professional before use.

DIRECTIONS

Place drops under tongue 30 minutes before/after meals. Adults and children 12 years and over: Take 10 drops up to 3 times per day. Consult a physician for use in children under 12 years of age.

OTHER INFORMATION

Tamper resistant. If seal is broken, do not use. After opening, close container tightly and store at room temperature away from heat.

INACTIVE INGREDIENTS

20% ethanol, purified water.

LABEL

Est 1985

Professional Formulas

Complementary Health

Rubber Gloves/Latex Detox

Homeopathic Remedy

2 FL. OZ. (59 mL)